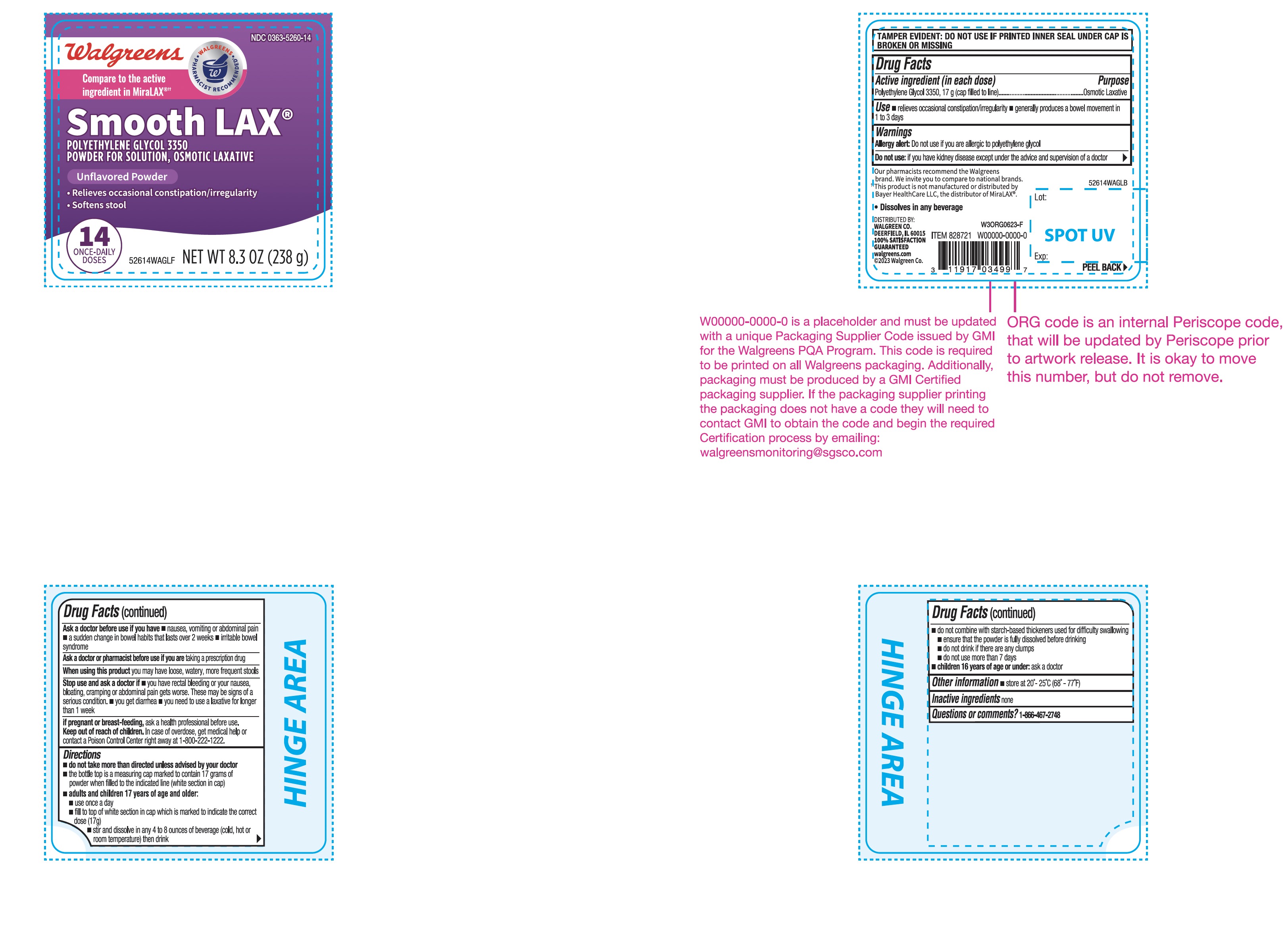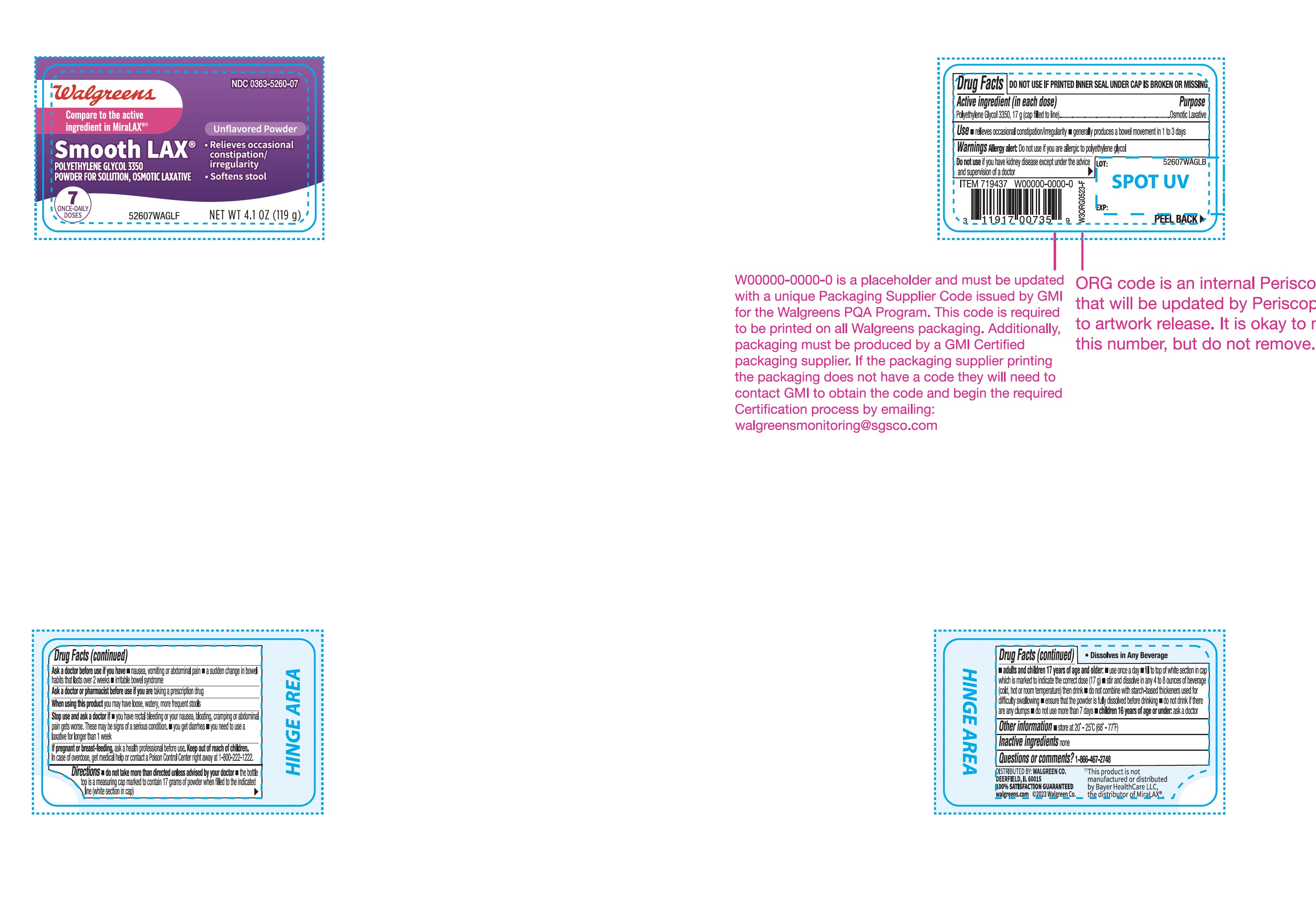 DRUG LABEL: Walgreens
NDC: 0363-5260 | Form: POWDER, FOR SOLUTION
Manufacturer: WALGREEN COMPANY
Category: otc | Type: HUMAN OTC DRUG LABEL
Date: 20251201

ACTIVE INGREDIENTS: POLYETHYLENE GLYCOL 3350 17 g/17 g

Walgreens Polyethylene Glycol 3350 Drug fact

Drug Facts

Active ingredient (in each dose)

Polyethylene Glycol 3350, 17 g (cap filled to line)

Purpose

Osmotic Laxative

Use

- relieves occasional constipation /irregularity
- generally produces a bowel movement in 1 to 3 days

Warnings

Allergy alert

Do not use if you are allergic to polyethylene glycol

DO NOT USE

Do not useif you have kidney disease, except under the advice and supervision of a doctor

Ask a doctor before use if you have

- nausea, vomiting or abdominal pain
- a sudden change in bowel habits that lasts over 2 weeks
- irritable bowel syndrome

Ask a doctor of pharmacist before use if you aretaking a prescription drug

WHEN USING

When using this productyou may have loose, watery, more frequent stools

Stop use and ask a doctor if

- you have rectal bleeding or your nausea, bloating or cramping or abdominal pain gets worse. These may be signs of a serious condition.
- you get diarrhea
- you need to use a laxative for longer than 1 week

PREGNANCY OR BREAST FEEDING

If pregnant or breast-feeding,ask a health professional before use.

KEEP OUT OF REACH OF CHILDREN

Keep out of the reach of children.In case of overdose, get medical help or contact a Poison Control Center right away at 1-800-222-1222.

Directions

- do not take more than directed unless advised by your doctor
- the bottle top is a measuring cap marked to contain 17 grams of powder when filled to the indicated line (white section in cap)
- adults and children 17 years of age and older:
  - use once a day
  - fill to top of white section in cap which is marked to indicate the correct dose (17 g)
  - stir and dissolve in any 4 to 8 ounces of beverage (cold, hot or room temperature) then drink
  - do not combine with starch-based thickeners used for difficulty swallowing
  - ensure that the powder is fully dissolved before drinking
  - do not drink if there are any clumps
  - do not use no more than 7 days
- children 16 years of age or under: ask a doctor

Other information

- store at 20°-25°C (68°-77°F)

Inactive ingredients

none

Questions or comments?

1-866-467-2748

TAMPER-EVIDENT: DO NOT USE IF FOIL SEAL UNDER CAP, PRINTED WITH "SEALED FOR YOUR PROTECTION" IS MISSING, OPEN OR BROKEN

PRINCIPAL DISPLAY PANEL

*Compare to the Active Ingredient in MiraLAX®

NDC 0363-5260-07

Polyethylene Glycol 3350,

Powder for Solution,

Osmotic Laxative

- Relieves Occasional Constipation/Irregularity
- Softens Stool

UNFLAVORED POWDER
7 ONCE-DAILY DOSES

NET WT 4.1 OZ (119 g)

*This product is not manufactured or distributed by Bayer HealthCare LLC, the distributer of MiraLAX®

Principal Display Panel

*Compare to the Active Ingredient in MiraLAX®

NDC 0363-5260-14

Polyethylene Glycol 3350,

Powder for Solution,

Osmotic Laxative

- Relieves Occasional Constipation/Irregularity
- Softens Stool

UNFLAVORED POWDER
14 ONCE-DAILY DOSES

NET WT 8.3 OZ (238 g)